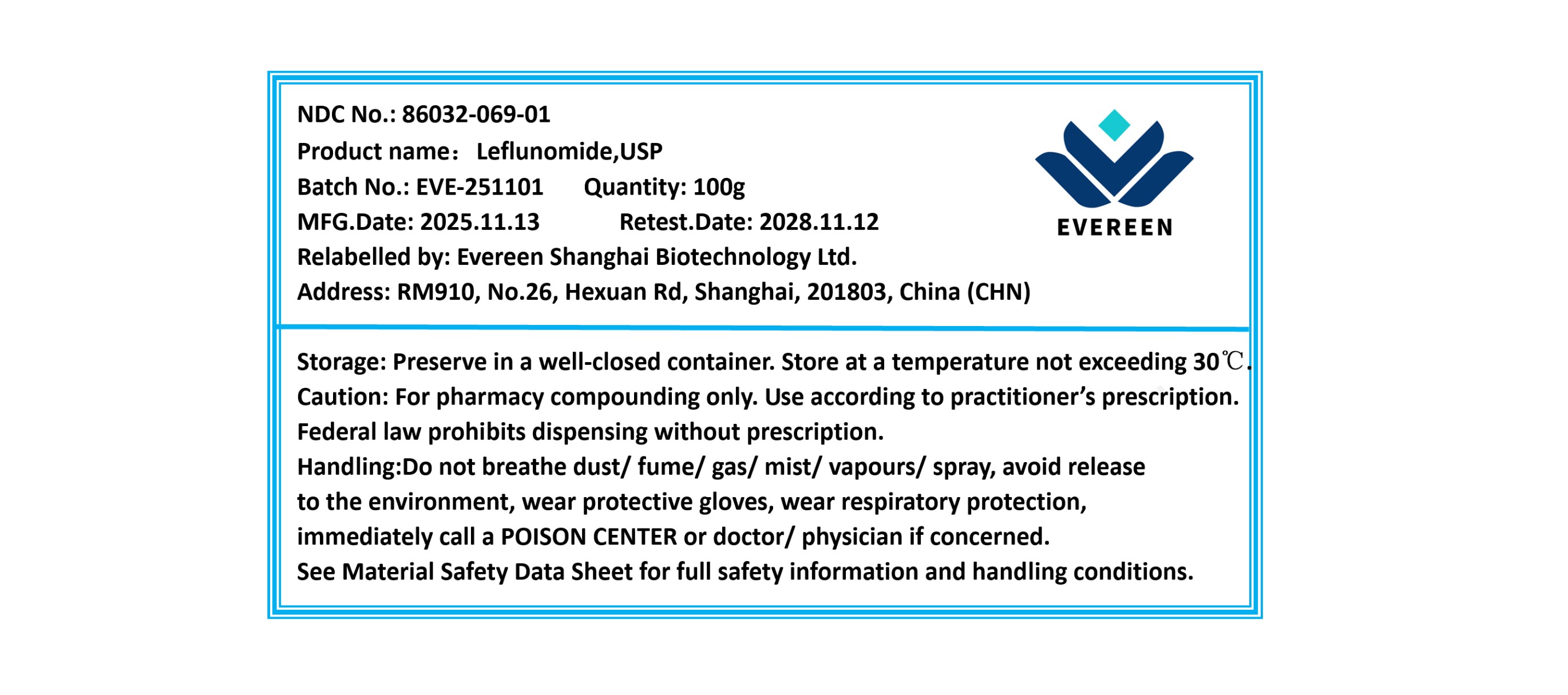 DRUG LABEL: Leflunomide
NDC: 86032-069 | Form: POWDER
Manufacturer: Evereen Shanghai Biotechnology Ltd.
Category: other | Type: BULK INGREDIENT - ANIMAL DRUG
Date: 20260115

ACTIVE INGREDIENTS: LEFLUNOMIDE 1 g/1 g

Leflunomide